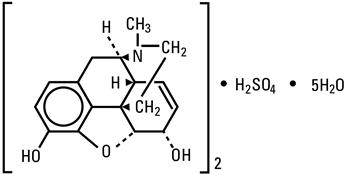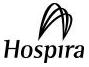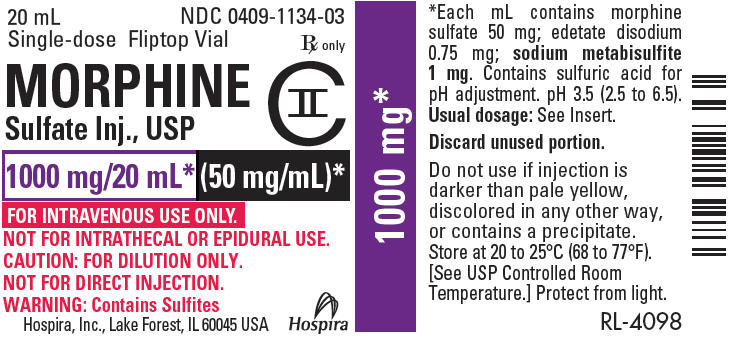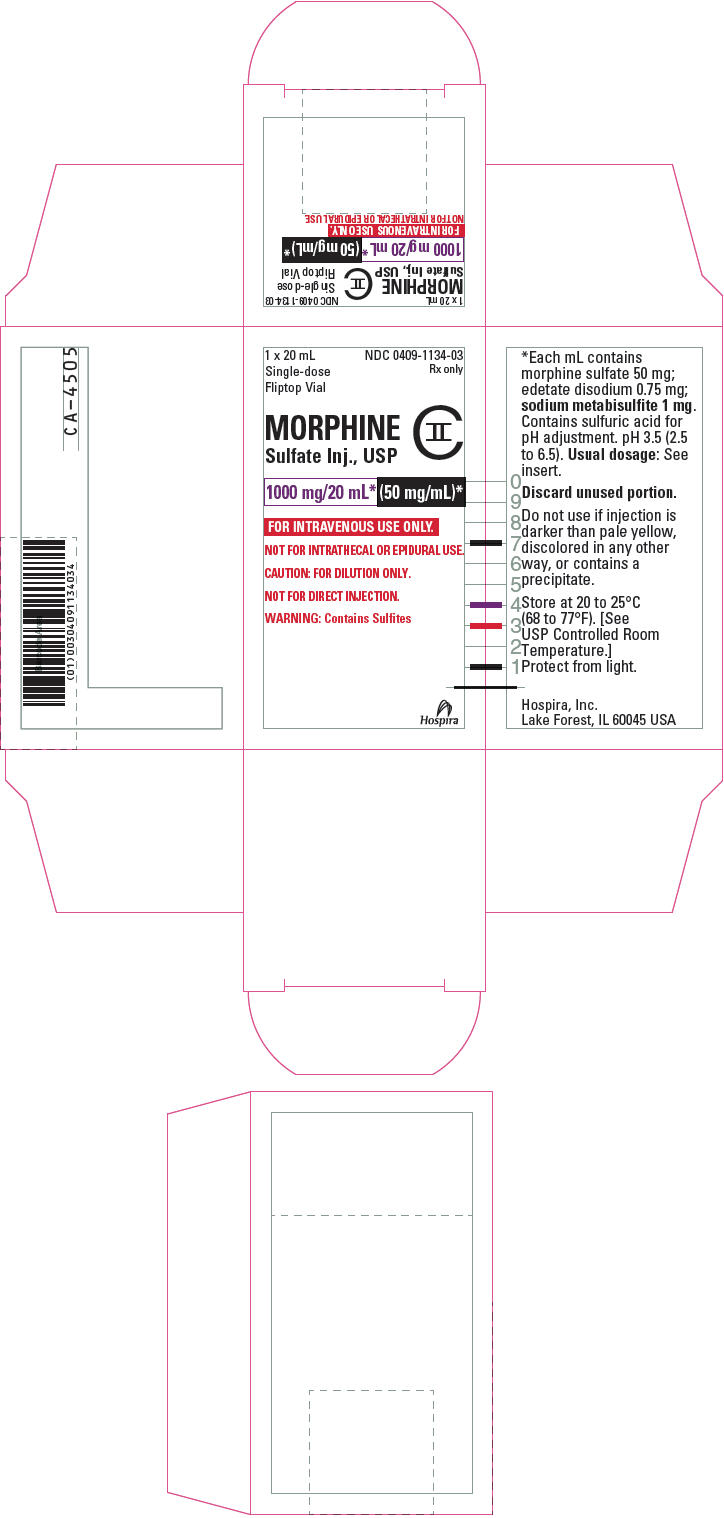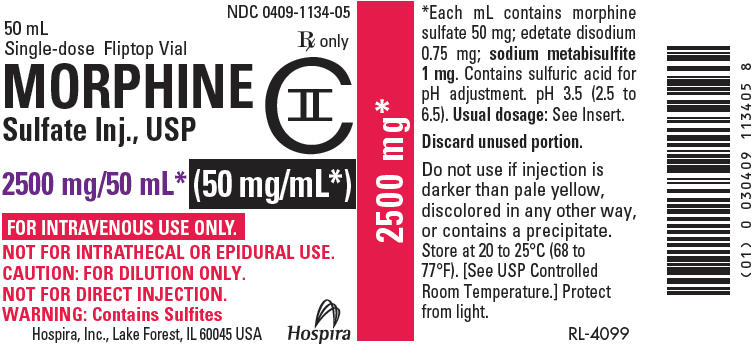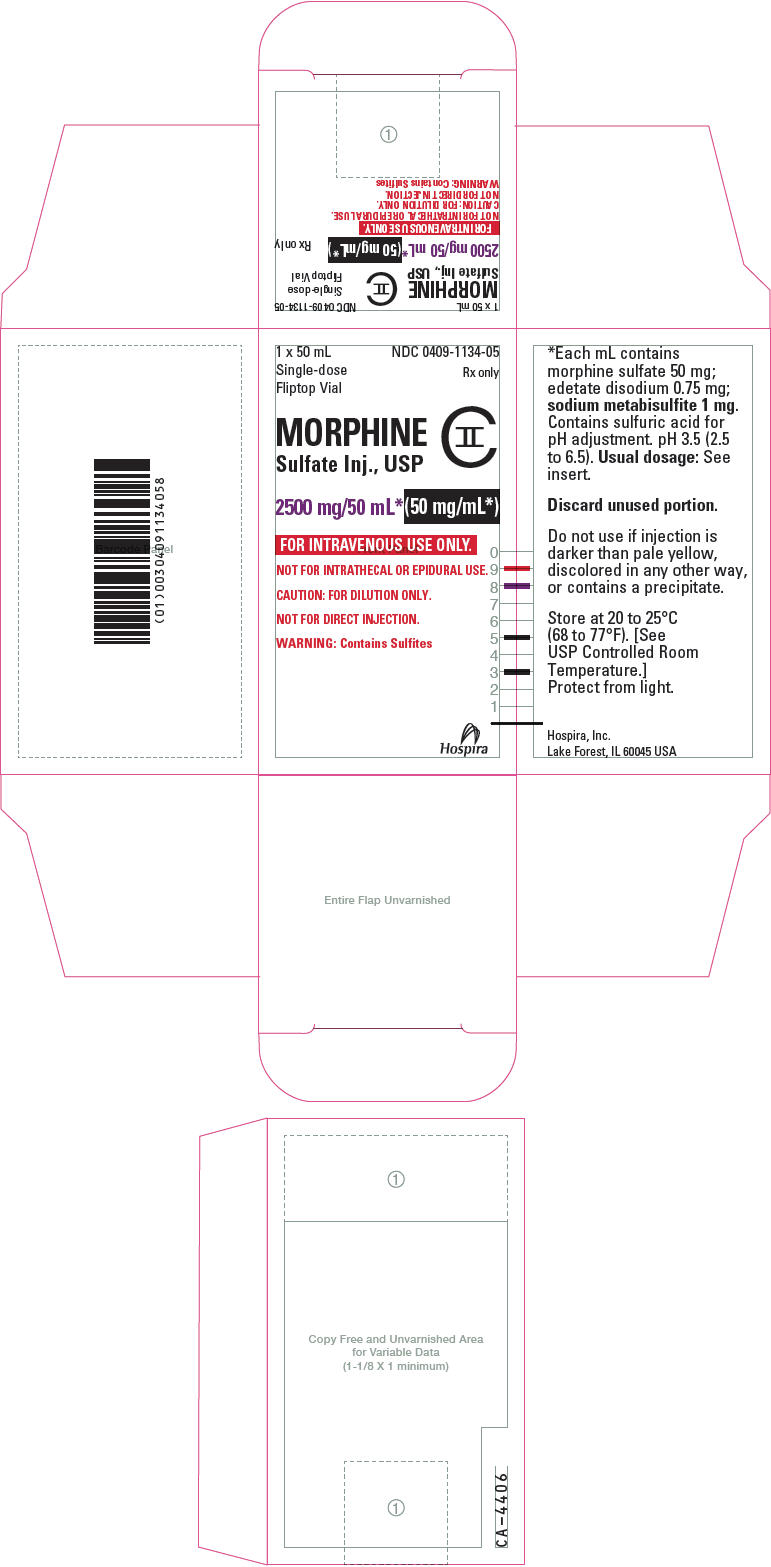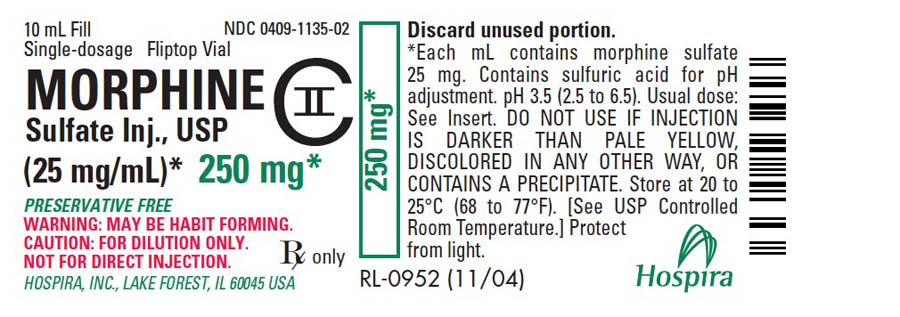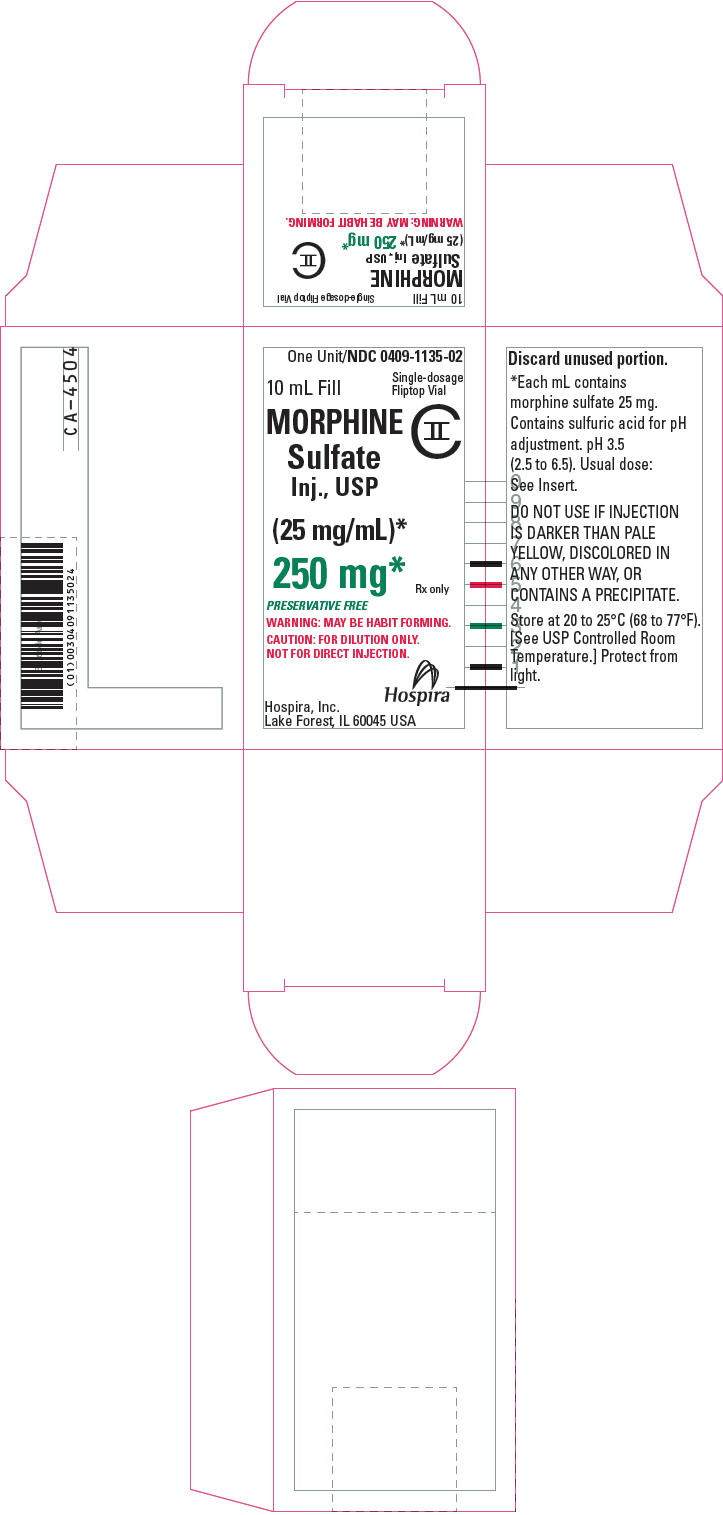 DRUG LABEL: Morphine Sulfate
NDC: 0409-1134 | Form: INJECTION, SOLUTION, CONCENTRATE
Manufacturer: Hospira, Inc.
Category: prescription | Type: HUMAN PRESCRIPTION DRUG LABEL
Date: 20211013
DEA Schedule: CII

ACTIVE INGREDIENTS: MORPHINE SULFATE 50 mg/1 mL

MORPHINE
SULFATE
Injection, USP
CII

FOR INTRAVENOUS USE ONLY
NOT FOR INTRATHECAL OR EPIDURAL USE

Fliptop Vial

Rx only

WARNING: ADDICTION, ABUSE, AND MISUSE; LIFE-THREATENING RESPIRATORY DEPRESSION; NEONATAL OPIOID WITHDRAWAL SYNDROME; and RISKS FROM CONCOMITANT USE WITH BENZODIAZEPINES OR OTHER CNS DEPRESSANTS

Addiction, Abuse, and Misuse

Morphine Sulfate Injection exposes patients and other users to the risks of opioid addiction, abuse, and misuse, which can lead to overdose and death. Assess each patient's risk prior to prescribing Morphine Sulfate Injection, and monitor all patients regularly for the development of these behaviors and conditions (see WARNINGS).

Life-Threatening Respiratory Depression

Serious, life-threatening, or fatal respiratory depression may occur with use of Morphine Sulfate Injection. Monitor for respiratory depression, especially during initiation of Morphine Sulfate Injection or following a dose increase. Because of delay in maximum central nervous system (CNS) effect with intravenously administered morphine (30 min), rapid intravenous administration may result in overdosing (see WARNINGS).

Neonatal Opioid Withdrawal Syndrome

Prolonged use of Morphine Sulfate Injection during pregnancy can result in neonatal opioid withdrawal syndrome, which may be life-threatening if not recognized and treated, and requires management according to protocols developed by neonatology experts. If opioid use is required for a prolonged period in a pregnant woman, advise the patient of the risk of neonatal opioid withdrawal syndrome and ensure that appropriate treatment will be available (see WARNINGS).

Risks From Concomitant Use With Benzodiazepines Or Other CNS Depressants

Concomitant use of opioids with benzodiazepines or other CNS depressants, including alcohol, may result in profound sedation, respiratory depression, coma, and death (see WARNINGS, Drug Interactions).

- Reserve concomitant prescribing of Morphine Sulfate Injection and benzodiazepines or other CNS depressants for use in patients for whom alternative treatment options are inadequate.
- Limit dosages and durations to the minimum required.
- Follow patients for signs and symptoms of respiratory depression and sedation.

DESCRIPTION

Morphine is a tertiary nitrogen base containing a phenanthrene nucleus; it has two hydroxyl groups, one phenolic and the other alcoholic (secondary). The sulfate salt occurs as white, feathery, silky crystals, cubical masses of crystals, or white, crystalline powder.

The chemical name of morphine sulfate is 7,8-didehydro-4,5α-epoxy-17-methylmorphinan-3,6α-diol sulfate (2:1) (salt), pentahydrate.

It has the following chemical structure:

(C17H19NO3)2 ∙ H2SO4 ∙ 5H2O M.W. 758.83

Morphine Sulfate Injection, USP is a sterile solution of morphine sulfate pentahydrate in Water for Injection, USP.

Morphine Sulfate Injection, USP is available in the following concentrations:

Each mL of Morphine Sulfate Injection, USP, Preservative Free (no bacteriostat or antioxidant added) contains 25 mg Morphine Sulfate in Water for Injection. Sulfuric acid added for adjustment of pH to 3.5 (2.5 to 6.5).

Each mL of Morphine Sulfate Injection, USP, (no bacteriostat added), contains 25 mg or 50 mg Morphine Sulfate, 0.75 mg Edetate Disodium, 1 mg Sodium Metabisulfite (added during manufacture) as an antioxidant, in Water for Injection. Sulfuric acid added for adjustment of pH to 3.5 (2.5 to 6.5).

NOTE: These products are intended for intravenous use only. They are not intended for intrathecal or epidural use. They are for use after dilution, not for direct infusion, and is intended as a single-dose unit. It contains no antimicrobial preservatives. When the dosing requirement is completed, the unused portion should be discarded in an appropriate manner.

CLINICAL PHARMACOLOGY

Mechanism of Action

Morphine is a full opioid agonist and is relatively selective for the mu-opioid receptor, although it can bind to other opioid receptors at higher doses. The principal therapeutic action of morphine is analgesia. Like all full opioid agonists, there is no ceiling effect for analgesia with morphine. Clinically, dosage is titrated to provide adequate analgesia and may be limited by adverse reactions, including respiratory and CNS depression.

The precise mechanism of the analgesic action is unknown. However, specific CNS opioid receptors for endogenous compounds with opioid-like activity have been identified throughout the brain and spinal cord and are thought to play a role in the analgesic effects of this drug.

Pharmacodynamics

Effects on the CNS

Morphine sulfate produces respiratory depression by direct action on brain stem respiratory centers. The respiratory depression involves a reduction in the responsiveness of the brain stem respiratory centers to both increases in carbon dioxide tension and electrical stimulation.

Morphine causes miosis, even in total darkness. Pinpoint pupils are a sign of opioid overdose but are not pathognomonic (e.g., pontine lesions of hemorrhagic or ischemic origins may produce similar findings). Marked mydriasis rather than miosis may be seen due to hypoxia in overdose situations.

Effects on the Gastrointestinal Tract and Other Smooth Muscle

Morphine causes a reduction in motility associated with an increase in smooth muscle tone in the antrum of the stomach duodenum. Digestion of food in the small intestine is delayed and propulsive contractions are decreased. Propulsive peristaltic waves in the colon are decreased, while tone may be increased to the point of spasm, resulting in constipation. Other opioid-induced effects may include a reduction in biliary and pancreatic secretions, spasm of sphincter of Oddi, and transient elevations in serum amylase.

Effects of the Cardiovascular System

Morphine produces peripheral vasodilation which may result in orthostatic hypotension or syncope. Manifestations of histamine release and/or peripheral vasodilation may include pruritus, flushing, red eyes, sweating, and/or orthostatic hypotension.

Effects on the Endocrine System

Opioids inhibit the secretion of adrenocorticotropic hormone (ACTH), cortisol, and luteinizing hormones (LH) in humans. They also stimulate prolactin, growth hormone (GH) secretion, and pancreatic secretion of insulin and glucagon.

Chronic use of opioids may influence the hypothalamic-pituitary-gonadal axis, leading to androgen deficiency that may manifest as low libido, impotence, erectile dysfunction, amenorrhea, or infertility. The causal role of opioids in the clinical syndrome of hypogonadism is unknown because the various medical, physical, lifestyle, and psychological stressors that may influence gonadal hormone levels have not been adequately controlled for in studies conducted to date (see ADVERSE REACTIONS).

Effects on the Immune System

Opioids have been shown to have a variety of effects on components of the immune system in in vitro and animal models. The clinical significance of these findings is unknown. Overall, the effects of opioids appear to be modestly immunosuppressive.

Concentration–Efficacy Relationships

The minimum effective analgesic concentration will vary widely among patients, especially among patients who have been previously treated with potent agonist opioids. The minimum effective analgesic concentration of morphine for any individual patient may increase over time due to an increase in pain, the development of a new pain syndrome, and/or the development of analgesic tolerance.

Concentration–Adverse Reaction Relationships

There is a relationship between increasing morphine sulfate plasma concentration and increasing frequency of dose-related opioid adverse reactions such as nausea, vomiting, CNS effects, and respiratory depression. In opioid-tolerant patients, the situation may be altered by the development of tolerance to opioid-related adverse reactions.

Pharmacokinetics

Distribution

Morphine has an apparent volume of distribution ranging from 1.0 to 4.7 L/kg after parenteral administration. Protein binding is low, about 36%, and muscle tissue binding is reported as 54%. A blood-brain barrier exists, and when morphine is introduced outside of the CNS, plasma concentrations of morphine remain higher than the corresponding CSF morphine levels.

Metabolism

The major pathway of clearance is hepatic glucuronidation to morphine-3-glucuronide, which is pharmacologically inactive.

Excretion

The major excretion path of the conjugate is through the kidneys, with about 10% in the feces. Morphine is also eliminated by the kidneys, 2 to 12% being excreted unchanged in the urine. Terminal half-life is commonly reported to vary from 1.5 to 4.5 hours, although the longer half-lives were obtained when morphine levels were monitored over protracted periods with very sensitive radioimmunoassay methods. The accepted elimination half-life in normal subjects is 1.5 to 2 hours.

Morphine has a total plasma clearance which ranges from 0.9 to 1.2 L/kg/h in post-operative patients, but shows considerable interindividual variation.

Specific Population

Sex

While evidence of greater post-operative Morphine Sulfate Injection consumption in men compared to women is present in the literature, clinically significant differences in analgesic outcomes and pharmacokinetic parameters have not been consistently demonstrated. Some studies have shown an increased sensitivity to the adverse effects of Morphine Sulfate Injection, including respiratory depression, in women compared to men.

Hepatic Impairment

Morphine pharmacokinetics are altered in patients with cirrhosis. Clearance was found to decrease with a corresponding increase in half-life. The M3G and M6G to morphine AUC ratios also decreased in these subjects, indicating diminished metabolic activity. Adequate studies of the pharmacokinetics of morphine in patients with severe hepatic impairment have not been conducted.

Renal Impairment

Morphine pharmacokinetics are altered in patients with renal failure. The AUC is increased and clearance is decreased and the metabolites, M3G and M6G, may accumulate to much higher plasma levels in patients with renal failure as compared to patients with normal renal function. Adequate studies of the pharmacokinetics of morphine in patients with severe renal impairment have not been conducted.

INDICATIONS AND USAGE

Morphine sulfate is indicated for the relief of severe pain. It is used preoperatively to sedate the patient and allay apprehension, facilitate anesthesia induction and reduce anesthetic dosage. It is likewise effective in the control of post-operative pain.

The use of morphine for the relief of pain should be reserved for the more severe manifestations of pain, as in myocardial infarction, severe injuries, or in severe chronic pain associated with terminal cancer after all non-narcotic analgesics have failed.

Effective analgesic therapy of severe chronic pain associated with terminal cancer continues to be a difficult problem. Intermittent administration of intramuscular morphine may be effective; however, the mode of therapy has significant limitations. Morphine has a short plasma half-life of 2.5 to 3.0 hours; therefore, frequent administration (every 1 to 2 hours) often becomes necessary to control severe pain associated with cancer. Tolerance develops to the analgesic effects and increasingly higher doses of morphine are required to produce analgesia. The higher morphine doses produce significant and often life-threatening side effects (see ADVERSE REACTIONS). The peak and trough effects produced by intermittent administration cause fluctuations in pain control. Repeated intramuscular injections are frequently unacceptable due to the lack of muscle mass in the debilitated patient, the tendency for bruising and bleeding at the injection site, and the anxiety and pain associated with the injection.

Continuous intravenous infusion of morphine (see DOSAGE AND ADMINISTRATION) has been employed as an alternative to traditional modes of administration. Lower doses of morphine produce uniform pain control because a steady morphine concentration is maintained. Titration of the dosage to the patient's needs is easily achieved by adjusting the infusion rate. The lag time between the patient's request for pain medication and administration of the dose and the amount of nursing time necessary for preparation and administration of frequent doses are reduced. The degree of respiratory depression and sedation may be decreased, and the anxiety experienced by the patient in anticipation of intramuscular administration is avoided. Some Investigators feel that tolerance to the analgesic effects may develop more slowly with continuous intravenous infusion.

In addition to analgesia, the drug may relieve anxiety and reduce left ventricular work by reducing preload pressure. Morphine is also used in the therapy of dyspnea associated with acute left ventricular and pulmonary edema. Care must be taken to avoid inducing respiratory depression in such patients.

For open-heart surgery, especially in high risk patients with cardiac disease, some anesthesiologists use morphine to produce anesthesia.

CONTRAINDICATIONS

Morphine Sulfate Injection is contraindicated in patients with:

- Significant respiratory depression (see WARNINGS)
- Acute or severe bronchial asthma in an unmonitored setting or in the absence of resuscitative equipment (see PRECAUTIONS)
- Concurrent use of monoamine oxidase inhibitors (MAOIs) or use of MAOIs within the last 14 days (see WARNINGS)
- Known or suspected gastrointestinal obstruction, including paralytic ileus (see PRECAUTIONS)
- Hypersensitivity to morphine (e.g., anaphylaxis) (see ADVERSE REACTIONS)

Because of its stimulating effect on the spinal cord, morphine should not be used in convulsive states, such as those occurring in status epilepticus, tetanus, and strychnine poisoning. Morphine is also contraindicated in the following conditions: heart failure secondary to chronic lung disease; cardiac arrhythmias; increased intracranial or cerebrospinal pressure; head injuries; brain tumor; acute alcoholism; and delirium tremens.

The use of bisulfites is contraindicated in asthmatics. Bisulfites and morphine may potentiate each other, preventing use by causing severe adverse reactions. Use with extreme caution in patients with chronic obstructive pulmonary disease or cor pulmonale, patients with substantially decreased respiratory reserve, and patients with pre-existing respiratory depression, hypoxia or hypercapnia. In such patients, even usual therapeutic doses of narcotics may decrease respiratory drive while simultaneously increasing airway resistance to the point of apnea.

WARNINGS

Contains Sulfites

The product which contains antioxidant (25 mg/mL and 50 mg/mL concentrations – see DESCRIPTION and HOW SUPPLIED), contains sodium metabisulfite, a sulfite that may cause allergic-type reactions, including anaphylactic symptoms and life-threatening or less severe asthmatic episodes in certain susceptible people. The overall prevalence of sulfite sensitivity in the general population is unknown and probably low. Sulfite sensitivity is seen more frequently in asthmatic than in nonasthmatic people.

Addiction, Abuse, and Misuse

Morphine Sulfate Injection contains morphine, a Schedule II controlled substance. As an opioid, Morphine Sulfate Injection exposes users to the risks of addiction, abuse, and misuse (see DRUG ABUSE AND DEPENDENCE).

Although the risk of addiction in any individual is unknown, it can occur in patients appropriately prescribed Morphine Sulfate Injection. Addiction can occur at recommended dosages and if the drug is misused or abused.

Assess each patient's risk for opioid addiction, abuse, or misuse prior to prescribing Morphine Sulfate Injection, and monitor all patients receiving morphine sulfate for the development of these behaviors and conditions. Risks are increased in patients with a personal or family history of substance abuse (including drug or alcohol abuse or addiction) or mental illness (e.g., major depression). The potential for these risks should not, however, prevent the proper management of pain in any given patient. Patients at increased risk may be prescribed opioids such as Morphine Sulfate Injection, but use in such patients necessitates intensive counseling about the risks and proper use of Morphine Sulfate Injection along with intensive monitoring for signs of addiction, abuse, and misuse.

Opioids are sought by drug abusers and people with addiction disorders and are subject to criminal diversion. Consider these risks when prescribing or dispensing Morphine Sulfate Injection. Strategies to reduce these risks include prescribing the drug in the smallest appropriate quantity. Contact local state professional licensing board or state controlled substances authority for information on how to prevent and detect abuse or diversion of this product.

Life-Threatening Respiratory Depression

Serious, life-threatening, or fatal respiratory depression has been reported with the use of opioids, even when used as recommended. Respiratory depression, if not immediately recognized and treated, may lead to respiratory arrest and death. Management of respiratory depression may include close observation, supportive measures, and use of opioid antagonists, depending on the patient's clinical status (see OVERDOSAGE). Carbon dioxide (CO2) retention from opioid-induced respiratory depression can exacerbate the sedating effects of opioids.

While serious, life-threatening, or fatal respiratory depression can occur at any time during the use of Morphine Sulfate Injection, the risk is greatest during the initiation of therapy or following a dosage increase. Because of a delay in the maximum CNS effect with intravenously administered Morphine Sulfate Injection (30 min), rapid administration may result in overdosing. The respiratory depression may be severe and could require intervention (see OVERDOSAGE). Monitor patients closely for respiratory depression, especially within the first 24–72 hours of initiating therapy with and following dosage increases of Morphine Sulfate Injection.

To reduce the risk of respiratory depression, proper dosing and titration of Morphine Sulfate Injection are essential (see DOSAGE AND ADMINISTRATION). Overestimating the Morphine Sulfate Injection dosage when converting patients from another opioid product can result in a fatal overdose with the first dose.

Opioids can cause sleep-related breathing disorders including central sleep apnea (CSA) and sleep-related hypoxemia. Opioid use increases the risk of CSA in a dose-dependent fashion. In patients who present with CSA, consider decreasing the opioid dosage using best practices for opioid taper (see DOSAGE AND ADMINISTRATION).

Neonatal Opioid Withdrawal Syndrome

Prolonged use of Morphine Sulfate Injection during pregnancy can result in withdrawal in the neonate. Neonatal opioid withdrawal syndrome, unlike opioid withdrawal syndrome in adults, may be life-threatening if not recognized and treated, and requires management according to protocols developed by neonatology experts. Observe newborns for signs of neonatal opioid withdrawal syndrome and manage accordingly. Advise pregnant women using opioids for a prolonged period of the risk of neonatal opioid withdrawal syndrome and ensure that appropriate treatment will be available (see Pregnancy).

Risks from Concomitant Use with Benzodiazepines or Other CNS Depressants

Profound sedation, respiratory depression, coma, and death may result from the concomitant use of Morphine Sulfate Injection with benzodiazepines or other CNS depressants (e.g., non-benzodiazepine sedatives/hypnotics, anxiolytics, tranquilizers, muscle relaxants, general anesthetics, antipsychotics, other opioids, alcohol). Because of these risks, reserve concomitant prescribing of these drugs for use in patients for whom alternative treatment options are inadequate.

Observational studies have demonstrated that concomitant use of opioid analgesics and benzodiazepines increases the risk of drug-related mortality compared to use of opioid analgesics alone. Because of similar pharmacological properties, it is reasonable to expect similar risk with the concomitant use of other CNS depressant drugs with opioid analgesics (see Drug Interactions).

If the decision is made to prescribe a benzodiazepine or other CNS depressant concomitantly with an opioid analgesic, prescribe the lowest effective dosages and minimum durations of concomitant use. In patients already receiving an opioid analgesic, prescribe a lower initial dose of the benzodiazepine or other CNS depressant than indicated in the absence of an opioid, and titrate based on clinical response. If an opioid analgesic is initiated in a patient already taking a benzodiazepine or other CNS depressant, prescribe a lower initial dose of the opioid analgesic, and titrate based on clinical response. Follow patients closely for signs and symptoms of respiratory depression and sedation.

Advise both patients and caregivers about the risks of respiratory depression and sedation when Morphine Sulfate Injection is used with benzodiazepines or other CNS depressants (including alcohol and illicit drugs). Advise patients not to drive or operate heavy machinery until the effects of concomitant use of the benzodiazepine or other CNS depressant have been determined. Screen patients for risk of substance use disorders, including opioid abuse and misuse, and warn them of the risk for overdose and death associated with the use of additional CNS depressants including alcohol and illicit drugs (see Drug Interactions).

Cardiovascular Instability

While low doses of intravenously administered morphine have little effect on cardiovascular stability, high doses are excitatory, resulting from sympathetic hyperactivity and increase in circulatory catecholamines. Have naloxone injection and resuscitative equipment immediately available for use in case of life-threatening or intolerable side effects and whenever morphine therapy is being initiated.

Interaction with Monoamine Oxidase Inhibitors

Monoamine oxidase inhibitors (MAOIs) may potentiate the effects of morphine, including respiratory depression, coma, and confusion. Morphine Sulfate Injection should not be used in patients taking MAOIs or within 14 days of stopping such treatment.

Adrenal Insufficiency

Cases of adrenal insufficiency have been reported with opioid use, more often following greater than one month of use. Presentation of adrenal insufficiency may include non-specific symptoms and signs including nausea, vomiting, anorexia, fatigue, weakness, dizziness, and low blood pressure. If adrenal insufficiency is suspected, confirm the diagnosis with diagnostic testing as soon as possible. If adrenal insufficiency is diagnosed, treat with physiologic replacement doses of corticosteroids. Wean the patient off of the opioid to allow adrenal function to recover and continue corticosteroid treatment until adrenal function recovers. Other opioids may be tried as some cases reported use of a different opioid without recurrence of adrenal insufficiency. The information available does not identify any particular opioids as being more likely to be associated with adrenal insufficiency.

Withdrawal

Avoid the use of mixed agonist/antagonist (e.g., pentazocine, nalbuphine, and butorphanol) or partial agonist (e.g., buprenorphine) analgesics in patients who are receiving a full opioid agonist analgesic, including Morphine Sulfate Injection. In these patients, mixed agonist/antagonist and partial agonist analgesics may reduce the analgesic effect and/or precipitate withdrawal symptoms.

When discontinuing Morphine Sulfate Injection in a physically-dependent patient, gradually taper the dosage. Do not abruptly discontinue Morphine Sulfate Injection in these patients (see DRUG ABUSE AND DEPENDENCE).

Risks of Driving and Operating Machinery

Morphine Sulfate Injection may impair the mental or physical abilities needed to perform potentially hazardous activities such as driving a car or operating machinery. Warn patients not to drive or operate dangerous machinery unless they are tolerant to the effects of Morphine Sulfate Injection and know how they will react to the medication.

PRECAUTIONS

General

Parenteral Therapy

Give by very slow intravenous injection, in the form of a diluted solution. Rapid intravenous injection of morphine and other narcotic analgesics increases the incidence of adverse reactions; severe respiratory depression, hypotension, apnea, peripheral circulatory collapse, cardiac arrest, and anaphylactic reactions have occurred. These preparations should not be administered intravenously unless a narcotic antagonist and facilities for assisted or controlled respiration are immediately available. When given parenterally, especially intravenously, the patient should be lying down. Use caution when injecting subcutaneously or intramuscularly in chilled areas or in patients with hypotension or shock, since impaired perfusion may prevent complete absorption. If repeated injections are administered, an excessive amount may be suddenly absorbed if normal circulation is reestablished.

Asthma and Other Respiratory Conditions

The use of bisulfites is contraindicated in asthmatics. Bisulfites and morphine may potentiate each other, preventing use by causing severe adverse reactions.

Use with extreme caution in patients with chronic obstructive pulmonary disease or cor pulmonale, patients with substantially decreased respiratory reserve, and patients with pre-existing respiratory depression, hypoxia or hypercapnia. In such patients, even usual therapeutic doses of narcotics may decrease respiratory drive while simultaneously increasing airway resistance to the point of apnea.

Supraventricular Tachycardias

Caution should be used in patients with atrial flutter and other supraventricular tachycardias due to a possible vagolytic action which may produce a significant increase in the ventricular response rate.

Renal and Hepatic Dysfunction

Morphine may have a prolonged duration and cumulative effect in patients with renal or hepatic dysfunction.

Convulsions

Morphine may aggravate pre-existing convulsive disorders. Convulsions may occur in individuals without a history of convulsive disorders if dosage is substantially escalated above recommended levels because of tolerance development.

Life-Threatening Respiratory Depression in Patients with Chronic Pulmonary Disease or in Elderly, Cachectic, or Debilitated Patients

The use of Morphine Sulfate Injection in patients with acute or severe bronchial asthma in an unmonitored setting or in the absence of resuscitative equipment is contraindicated.

Patients with Chronic Pulmonary Disease

Morphine Sulfate Injection-treated patients with significant chronic obstructive pulmonary disease or cor pulmonale, and those with a substantially decreased respiratory reserve, hypoxia, hypercapnia, or pre-existing respiratory depression are at increased risk of decreased respiratory drive including apnea, even at recommended dosages of Morphine Sulfate Injection (see WARNINGS).

Elderly, Cachectic, or Debilitated Patients

Life-threatening respiratory depression is more likely to occur in elderly, cachectic, or debilitated patients because they may have altered pharmacokinetics or altered clearance compared to younger, healthier patients (see WARNINGS).

Caution must be exercised in elderly and debilitated patients and in patients who are known to be sensitive to CNS depressants, including those with cardiovascular or pulmonary disease, myxedema, cerebral arteriosclerosis, emphysema, fever, bronchial asthma, kyphoscoliosis, Addison's disease, prostatic hypertrophy or urethral stricture, toxic psychosis.

Monitor such patients closely, particularly when initiating and titrating Morphine Sulfate Injection and when Morphine Sulfate Injection is given concomitantly with other drugs that depress respiration (see WARNINGS). Alternatively, consider the use of non-opioid analgesics in these patients.

Risks of Use in Patients with Increased Intracranial Pressure, Brain Tumors, Head Injury, or Impaired Consciousness

In patients who may be susceptible to the intracranial effects of CO2 retention (e.g., those with evidence of increased intracranial pressure or brain tumors), Morphine Sulfate Injection may reduce respiratory drive, and the resultant CO2 retention can further increase intracranial pressure. Monitor such patients for signs of sedation and respiratory depression, particularly when initiating therapy with Morphine Sulfate Injection.

Opioids may also obscure the clinical course in a patient with a head injury. Avoid the use of Morphine Sulfate Injection in patients with impaired consciousness or coma.

Severe Hypotension

Morphine Sulfate Injection may cause severe hypotension including orthostatic hypotension and syncope in ambulatory patients. There is increased risk in patients whose ability to maintain blood pressure has already been compromised by a reduced blood volume or concurrent administration of certain CNS depressant drugs (e.g., phenothiazines or general anesthetics) (see Drug Interactions). Monitor these patients for signs of hypotension after initiating or titrating the dosage of Morphine Sulfate Injection. In patients with circulatory shock, Morphine Sulfate Injection may cause vasodilation that can further reduce cardiac output and blood pressure. Avoid the use of Morphine Sulfate Injection in patients with circulatory shock.

Risks of Use in Patients with Gastrointestinal Conditions

Morphine Sulfate Injection is contraindicated in patients with known or suspected gastrointestinal obstruction, including paralytic ileus.

The morphine in Morphine Sulfate Injection may cause spasm of the sphincter of Oddi. Opioids may cause increases in serum amylase. Monitor patients with biliary tract disease, including acute pancreatitis, for worsening symptoms.

The administration of morphine or other narcotics may obscure the diagnosis or clinical course in patients with acute abdominal conditions. Use also with caution in patients with gastrointestinal hemorrhage, ulcerative colitis, or recent gastrointestinal or urinary tract surgery.

Increased Risk of Seizures in Patients with Seizure Disorders

The morphine in Morphine Sulfate Injection may increase the frequency of seizures in patients with seizure disorders, and may increase the risk of seizures occurring in other clinical settings associated with seizures. Monitor patients with a history of seizure disorders for worsened seizure control during Morphine Sulfate Injection therapy.

Patient Information

Serotonin Syndrome

Opioids can cause a rare but potentially life-threatening condition resulting from concomitant administration of serotonergic drugs. Instruct patients to inform their physicians if they are taking, or plan to take serotonergic medications (see Drug Interactions).

Constipation

Advise patients of the potential for severe constipation, including management instructions and when to seek medical attention (see ADVERSE REACTIONS).

Drug Interactions

Morphine may increase the anticoagulant activity of coumarin and other anticoagulants.

When morphine is to be administered to patients receiving propiomazine (Largon), the dose of morphine should be reduced by one-quarter to one-half.

Atropine antagonizes morphine respiratory depression. Levallorphan and nalorphine antagonize morphine actions, principally the respiratory depression.

Table 1: Clinically Significant Drug Interactions with Morphine Sulfate Injection
Benzodiazepines and Other CNS Depressants
Clinical Impact: | Due to additive pharmacologic effect, the concomitant use of benzodiazepines or other CNS depressants, including alcohol, can increase the risk of hypotension, respiratory depression, profound sedation, coma, and death.
Intervention: | Reserve concomitant prescribing of these drugs for use in patients for whom alternative treatment options are inadequate. Limit dosages and durations to the minimum required. Follow patients closely for signs of respiratory depression and sedation (see WARNINGS).
Examples: | Benzodiazepines and other sedatives/hypnotics, anxiolytics, tranquilizers, muscle relaxants, general anesthetics, antipsychotics, other opioids, alcohol.
Serotonergic Drugs
Clinical Impact: | The concomitant use of opioids with other drugs that affect the serotonergic neurotransmitter system has resulted in serotonin syndrome.
Intervention: | If concomitant use is warranted, carefully observe the patient, particularly during treatment initiation and dose adjustment. Discontinue Morphine Sulfate Injection if serotonin syndrome is suspected.
Examples: | Selective serotonin reuptake inhibitors (SSRIs), serotonin and norepinephrine reuptake inhibitors (SNRIs), tricyclic antidepressants (TCAs), triptans, 5-HT3 receptor antagonists, drugs that affect the serotonin neurotransmitter system (e.g., mirtazapine, trazodone, tramadol), certain muscle relaxants (i.e., cyclobenzaprine, metaxalone), monoamine oxidase (MAO) inhibitors (those intended to treat psychiatric disorders and also others, such as linezolid and intravenous methylene blue).
Monoamine Oxidase Inhibitors (MAOIs)
Clinical Impact: | MAOI interactions with opioids may manifest as serotonin syndrome or opioid toxicity (e.g., respiratory depression, coma) (see WARNINGS).
Intervention: | Do not use Morphine Sulfate Injection in patients taking MAOIs or within 14 days of stopping such treatment. If urgent use of an opioid is necessary, use test doses and frequent titration of small doses of other opioids (such as oxycodone, hydrocodone, oxymorphone, or buprenorphine) to treat pain while closely monitoring blood pressure and signs and symptoms of CNS and respiratory depression.
Examples: | phenelzine, tranylcypromine, linezolid
Mixed Agonist/Antagonist and Partial Agonist Opioid Analgesics
Clinical Impact: | May reduce the analgesic effect of Morphine Sulfate Injection and/or precipitate withdrawal symptoms.
Intervention: | Avoid concomitant use.
Examples: | butorphanol, nalbuphine, pentazocine, buprenorphine
Muscle Relaxants
Clinical Impact: | Morphine may enhance the neuromuscular blocking action of skeletal muscle relaxants and produce an increased degree of respiratory depression.
Intervention: | Monitor patients for signs of respiratory depression that may be greater than otherwise expected and decrease the dosage of Morphine Sulfate Injection and/or the muscle relaxant as necessary.
Cimetidine
Clinical Impact: | Concomitant administration of Morphine Sulfate Injection and cimetidine has been reported to precipitate apnea, confusion, and muscle twitching in an isolated report.
Intervention: | Monitor patients for increased respiratory and CNS depression when receiving cimetidine concomitantly with Morphine Sulfate Injection.
Diuretics
Clinical Impact: | Opioids can reduce the efficacy of diuretics by inducing the release of antidiuretic hormone.
Intervention: | Monitor patients for signs of diminished diuresis and/or effects on blood pressure and increase the dosage of the diuretic as needed.
Anticholinergic Drugs
Clinical Impact: | The concomitant use of anticholinergic drugs may increase risk of urinary retention and/or severe constipation, which may lead to paralytic ileus.
Intervention: | Monitor patients for signs of urinary retention or reduced gastric motility when Morphine Sulfate Injection is used concomitantly with anticholinergic drugs.
Oral P2Y12 Inhibitors
Clinical Impact: | The co-administration of oral P2Y12 inhibitors and intravenous morphine sulfate can decrease the absorption and peak concentration of oral P2Y12 inhibitors and delay the onset of the antiplatelet effect.
Intervention: | Consider the use of a parenteral antiplatelet agent in the setting of acute coronary syndrome requiring co-administration of intravenous morphine sulfate.
Examples: | clopidogrel, prasugrel, ticagrelor

Carcinogenesis, Mutagenesis, Impairment of Fertility

Carcinogenesis

Long-term studies in animals to evaluate the carcinogenic potential of morphine have not been conducted.

Mutagenesis

No formal studies to assess the mutagenic potential of morphine have been conducted. In the published literature, morphine was found to be mutagenic in vitro increasing DNA fragmentation in human T-cells. Morphine was also reported to be mutagenic in the in vivo mouse micronucleus assay and positive for the induction of chromosomal aberrations in mouse spermatids and murine lymphocytes. Mechanistic studies suggest that the in vivo clastogenic effects reported with morphine in mice may be related to increases in glucocorticoid levels produced by morphine in these species. In contrast to the above positive findings, in vitro studies in the literature have also shown that morphine did not induce chromosomal aberrations in human leukocytes or translocations or lethal mutations in Drosophila.

Impairment of Fertility

No formal nonclinical studies to assess the potential of morphine to impair fertility have been conducted.

Several nonclinical studies from the literature have demonstrated adverse effects on male fertility in the rat from exposure to morphine. One study in which male rats were administered morphine sulfate subcutaneously prior to mating (up to 30 mg/kg twice daily) and during mating (20 mg/kg twice daily) with untreated females, a number of adverse reproductive effects including reduction in total pregnancies and higher incidence of pseudopregnancies at 20 mg/kg/day (3.2 times the human daily dose-HDD of 60 mg based on body surface area) were reported.

Studies from the literature have also reported changes in hormonal levels in male rats (i.e., testosterone, LH) following treatment with morphine at 10 mg/kg/day or greater (1.6 times the HDD).

Female rats that were administered morphine sulfate intraperitoneally prior to mating exhibited prolonged estrous cycles at 10 mg/kg/day (1.6 times the HDD).

Exposure of adolescent male rats to morphine has been associated with delayed sexual maturation and following mating to untreated females, smaller litters, increased pup mortality, and/or changes in reproductive endocrine status in adult male offspring have been reported (estimated 5 times the plasma levels at the HDD).

Pregnancy

Risk Summary

Prolonged use of opioid analgesics during pregnancy can cause neonatal opioid withdrawal syndrome (see WARNINGS). There are no available data with Morphine Sulfate Injection in pregnant women to inform a drug-associated risk for major birth defects and miscarriage. Published studies with morphine use during pregnancy have not reported a clear association with morphine and major birth defects (see Human Data). In published animal reproduction studies, morphine administered subcutaneously during the early gestational period produced neural tube defects (i.e., exencephaly and cranioschisis) at 5 and 16 times the HDD of 60 mg based on body surface area in hamsters and mice, respectively, lower fetal body weight and increased incidence of abortion at 0.4 times the HDD in the rabbit, growth retardation at 6 times the HDD in the rat, and axial skeletal fusion and cryptorchidism at 16 times the HDD in the mouse. Administration of morphine sulfate to pregnant rats during organogenesis and through lactation resulted in cyanosis, hypothermia, decreased brain weights, pup mortality, decreased pup body weights, and adverse effects on reproductive tissues at 3–4 times the HDD; and long-term neurochemical changes in the brain of offspring which correlate with altered behavioral responses that persist through adulthood at exposures comparable to and less than the HDD (see Animal Data). Based on animal data, advise pregnant women of the potential risk to a fetus.

The estimated background risk of major birth defects and miscarriage for the indicated population is unknown. All pregnancies have a background risk of birth defect, loss, or other adverse outcomes. In the U.S. general population, the estimated background risk of major birth defects and miscarriage in clinically recognized pregnancies is 2–4% and 15–20%, respectively.

Clinical Considerations

Fetal/Neonatal Adverse Reactions

Prolonged use of opioid analgesics during pregnancy for medical or non-medical purposes can result in physical dependence in the neonate and neonatal opioid withdrawal syndrome shortly after birth. Neonatal opioid withdrawal syndrome presents as irritability, hyperactivity and abnormal sleep pattern, high pitched cry, tremor, vomiting, diarrhea, and failure to gain weight. The onset, duration, and severity of neonatal withdrawal syndrome vary based on the specific opioid used, duration of use, timing and amount of last maternal use, and rate of elimination of the drug by the newborn. Observe newborns for signs of neonatal opioid withdrawal syndrome and manage accordingly (see WARNINGS).

Labor or Delivery

Opioids cross the placenta and may produce respiratory depression and psycho-physiologic effects in neonates. An opioid antagonist, such as naloxone, must be available for reversal of opioid-induced respiratory depression in the neonate. Morphine Sulfate Injection is not recommended for use in women during and immediately prior to labor, when use of shorter-acting analgesics or other analgesic techniques are more appropriate. Opioid analgesics, including Morphine Sulfate Injection, can prolong labor through actions that temporarily reduce the strength, duration, and frequency of uterine contractions. However, this effect is not consistent and may be offset by an increased rate of cervical dilatation, which tends to shorten labor. Monitor neonates exposed to opioid analgesics during labor for signs of excess sedation and respiratory depression.

Data

Human Data

The results from a population-based prospective cohort, including 70 women exposed to morphine during the first trimester of pregnancy and 448 women exposed to morphine at any time during pregnancy, indicate no increased risk for congenital malformations. However, these studies cannot definitely establish the absence of any risk because of methodological limitations, including small sample size and non-randomized study design.

Animal Data

Formal reproductive and developmental toxicology studies for morphine have not been conducted. Exposure margins for the following published study reports are based on the HDD of 60 mg morphine using a body surface area comparison.

Neural tube defects (exencephaly and cranioschisis) were noted following subcutaneous administration of morphine sulfate (35–322 mg/kg) on Gestation Day 8 to pregnant hamsters (4.7 to 43.5 times the HDD). A no adverse effect level was not defined in this study and the findings cannot be clearly attributed to maternal toxicity. Neural tube defects (exencephaly), axial skeletal fusions, and cryptorchidism were reported following a single subcutaneous injection of morphine sulfate to pregnant mice (100–500 mg/kg) on Gestation Day 8 or 9 at 200 mg/kg or greater (16 times the HDD) and fetal resorption at 400 mg/kg or higher (32 times the HDD). No adverse effects were noted following 100 mg/kg morphine in this model (8 times the HDD). In one study, following continuous subcutaneous infusion of doses greater than or equal to 2.72 mg/kg to mice (0.2 times the HDD), exencephaly, hydronephrosis, intestinal hemorrhage, split supraoccipital, malformed sternebrae, and malformed xiphoid were noted. The effects were reduced with increasing daily dose; possibly due to rapid induction of tolerance under these infusion conditions. The clinical significance of this report is not clear.

Decreased fetal weights were observed in pregnant rats treated with 20 mg/kg/day morphine sulfate (3.2 times the HDD) from Gestation Day 7 to 9. There was no evidence of malformations despite maternal toxicity (10% mortality). In a second rat study, decreased fetal weight and increased incidences of growth retardation were noted at 35 mg/kg/day (5.7 times the HDD) and there was a reduced number of fetuses at 70 mg/kg/day (11.4 times the HDD) when pregnant rats were treated with 10, 35, or 70 mg/kg/day morphine sulfate via continuous infusion from Gestation Day 5 to 20. There was no evidence of fetal malformations or maternal toxicity.

An increased incidence of abortion was noted in a study in which pregnant rabbits were treated with 2.5 (0.8 times the HDD) to 10 mg/kg morphine sulfate via subcutaneous injection from Gestation Day 6 to 10. In a second study, decreased fetal body weights were reported following treatment of pregnant rabbits with increasing doses of morphine (10–50 mg/kg/day) during the pre-mating period and 50 mg/kg/day (16 times the HDD) throughout the gestation period. No overt malformations were reported in either publication; although only limited endpoints were evaluated.

In published studies in rats, exposure to morphine during gestation and/or lactation periods is associated with: decreased pup viability at 12.5 mg/kg/day or greater (2 times the HDD); decreased pup body weights at 15 mg/kg/day or greater (2.4 times the HDD); decreased litter size, decreased absolute brain and cerebellar weights, cyanosis, and hypothermia at 20 mg/kg/day (3.2 times the HDD); alteration of behavioral responses (play, social-interaction) at 1 mg/kg/day or greater (0.2 times the HDD); alteration of maternal behaviors (e.g., decreased nursing and pup retrievals) in mice at 1 mg/kg or higher (0.08 times the HDD) and rats at 1.5 mg/kg/day or higher (0.2 times the HDD); and a host of behavioral abnormalities in the offspring of rats, including altered responsiveness to opioids at 4 mg/kg/day (0.7 times the HDD) or greater.

Fetal and/or postnatal exposure to morphine in mice and rats has been shown to result in morphological changes in fetal and neonatal brain and neuronal cell loss, alteration of a number of neurotransmitter and neuromodulator systems, including opioid and non-opioid systems, and impairment in various learning and memory tests that appear to persist into adulthood. These studies were conducted with morphine treatment usually in the range of 4 to 20 mg/kg/day (0.7 to 3.2 times the HDD).

Additionally, delayed sexual maturation and decreased sexual behaviors in female offspring at 20 mg/kg/day (3.2 times the HDD), and decreased plasma and testicular levels of LH and testosterone, decreased testes weights, seminiferous tubule shrinkage, germinal cell aplasia, and decreased spermatogenesis in male offspring were also observed at 20 mg/kg/day (3.2 times the HDD). Decreased litter size and viability were observed in the offspring of male rats that were intraperitoneally administered morphine sulfate for 1 day prior to mating at 25 mg/kg/day (4.1 times the HDD) and mated to untreated females. Decreased viability and body weight and/or movement deficits in both first and second generation offspring were reported when male mice were treated for 5 days with escalating doses of 120 to 240 mg/kg/day morphine sulfate (9.7 to 19.5 times the HDD) or when female mice treated with escalating doses of 60 to 240 mg/kg/day (4.9 to 19.5 times the HDD) followed by a 5-day treatment-free recovery period prior to mating. Similar multigenerational findings were also seen in female rats pre-gestationally treated with escalating doses of 10 to 22 mg/kg/day morphine (1.6 to 3.6 times the HDD).

Lactation

Risk Summary

Morphine is present in breast milk. Published lactation studies report variable concentrations of morphine in breast milk with administration of immediate-release morphine to nursing mothers in the early postpartum period with a milk-to-plasma morphine AUC ratio of 2.5:1 measured in one lactation study. However, there is insufficient information to determine the effects of morphine on the breastfed infant and the effects of morphine on milk production. Lactation studies have not been conducted with Morphine Sulfate Injection, and no information is available on the effects of the drug on the breastfed infant or the effects of the drug on milk production.

The developmental and health benefits of breastfeeding should be considered along with the mother's clinical need for Morphine Sulfate Injection, and any potential adverse effects on the breastfed infant from Morphine Sulfate Injection, or from the underlying maternal condition.

Clinical Considerations

Monitor infants exposed to Morphine Sulfate Injection, through breast milk for excess sedation and respiratory depression. Withdrawal symptoms can occur in breastfed infants when maternal administration of morphine is stopped, or when breastfeeding is stopped.

Females and Males of Reproductive Potential

Infertility

Chronic use of opioids may cause reduced fertility in females and males of reproductive potential. It is not known whether these effects on fertility are reversible (see CLINICAL PHARMACOLOGY).

In published animal studies, morphine administration adversely effected fertility and reproductive endpoints in male rats and prolonged estrus cycle in female rats (see Carcinogenesis, Mutagenesis, Impairment of Fertility).

Pediatric Use

The safety and effectiveness of Morphine Sulfate Injection in pediatric patients below the age of 18 have not been established.

Geriatric Use

The pharmacodynamic effects of morphine in the elderly are more variable than in the younger population. Older patients will vary widely in the effective initial dose, rate of development of tolerance and the frequency and magnitude of associated adverse effects as the dose is increased. Initial elderly patients (aged 65 years or older) may have increased sensitivity to morphine. In general, use caution when selecting a dosage for an elderly patient, usually starting at the low end of the dosing range, reflecting the greater frequency of decreased hepatic, renal, or cardiac function and of concomitant disease or other drug therapy.

Respiratory depression is the chief risk for elderly patients treated with opioids, and has occurred after large initial doses were administered to patients who were not opioid-tolerant or when opioids were co-administered with other agents that depress respiration. Titrate the dosage of Morphine Sulfate Injection slowly in geriatric patients and monitor closely for signs of CNS and respiratory depression (see PRECAUTIONS).

Morphine is known to be substantially excreted by the kidney, and the risk of adverse reactions to this drug may be greater in patients with impaired renal function. Because elderly patients are more likely to have decreased renal function, care should be taken in dose selection, and it may be useful to monitor renal function.

Hepatic Impairment

Morphine pharmacokinetics have been reported to be significantly altered in patients with cirrhosis. Start these patients with a lower than normal dosage of Morphine Sulfate Injection and titrate slowly while monitoring for signs of respiratory depression, sedation, and hypotension (see CLINICAL PHARMACOLOGY).

Renal Impairment

Morphine pharmacokinetics are altered in patients with renal failure. Start these patients with a lower than normal dosage of Morphine Sulfate Injection and titrate slowly while monitoring for signs of respiratory depression, sedation, and hypotension (see CLINICAL PHARMACOLOGY).

ADVERSE REACTIONS

The following serious adverse reactions are described, or described in greater detail, in other sections:

- Addiction, Abuse, and Misuse (see WARNINGS)
- Life-Threatening Respiratory Depression (see WARNINGS)
- Neonatal Opioid Withdrawal Syndrome (see WARNINGS)
- Interactions with Benzodiazepines or Other CNS Depressants (see WARNINGS)
- Cardiovascular Instability (see WARNINGS)
- Adrenal Insufficiency (see WARNINGS)
- Severe Hypotension (see PRECAUTIONS)
- Gastrointestinal Adverse Reactions (see PRECAUTIONS)
- Seizures (see PRECAUTIONS)
- Withdrawal (see WARNINGS)

The following adverse reactions associated with the use of morphine were identified in clinical studies or postmarketing reports. Because some of these reactions were reported voluntarily from a population of uncertain size, it is not always possible to reliably estimate their frequency or establish a causal relationship to drug exposure.

Serious adverse reactions associated with Morphine Sulfate Injection included respiratory depression, apnea, and to a lesser degree, circulatory depression, respiratory arrest, shock, and cardiac arrest. Rarely, anaphylactoid reactions have been reported when morphine or other phenanthrene alkaloids of opium are administered intravenously.

The most frequently observed adverse reactions included sedation, lightheadedness, dizziness, nausea, vomiting, constipation, and diaphoresis.

Lightheadedness, dizziness, sedation, nausea, vomiting and sweating seem to be more prominent in ambulatory patients and in those who are not suffering from severe pain. In such individuals, lower doses are advisable.

Other possible adverse reactions included:

CNS – Euphoria, dysphoria, weakness, headache, agitation, tremor, uncoordinated muscle movements, visual disturbances, transient hallucinations, disorientation, delirium, somnolence, drowsiness, miosis, pinpoint pupils, coma, insomnia, impairment of mental and physical performance, mental clouding, lethargy, anxiety, fear, psychic dependence, mood changes, confusion.

Gastrointestinal – Constipation, biliary tract spasm, dry mouth, anorexia. Patients with chronic ulcerative colitis may experience increased colonic motility; toxic dilatation has been reported in patients with acute ulcerative colitis.

Cardiovascular – Tachycardia, bradycardia, palpitation, faintness, syncope, orthostatic hypotension, peripheral circulatory collapse, hypotension, phlebitis following intravenous injection.

Genitourinary – Oliguria and urinary retention or hesitancy; an antidiuretic effect has been reported; ureteral spasm and spasm of vesical sphincters, reduced libido and/or potency.

Allergic – Pruritus, urticaria, skin rashes, edema, and (rarely) hemorrhagic urticaria. Flare over the vein with intravenous injection may occur. Anaphylactoid reactions have been reported following intravenous administration. An isolated case of thrombocytopenia has been reported to be induced by morphine.

Other – Opioid-induced histamine release may be responsible for the flushing of the face, diaphoresis, and pruritus often seen with these drugs. Wheals and urticaria at the site of injection are probably related to histamine release. Local tissue irritation, pain, and induration have been reported following repeated subcutaneous injection. Morphine may alter temperature regulation in susceptible individuals and will depress the cough reflex.

Serotonin syndrome: Cases of serotonin syndrome, a potentially life-threatening condition, have been reported during concomitant use of opioids with serotonergic drugs.

Adrenal insufficiency: Cases of adrenal insufficiency have been reported with opioid use, more often following greater than one month of use.

Anaphylaxis: Anaphylaxis has been reported with ingredients contained in Morphine Sulfate Injection.

Androgen deficiency: Cases of androgen deficiency have occurred with chronic use of opioids (see CLINICAL PHARMACOLOGY).

DRUG ABUSE AND DEPENDENCE

Controlled Substance

Morphine Sulfate Injection contains morphine, a Schedule II controlled substance.

Abuse

Morphine Sulfate Injection contains morphine, a substance with a high potential for abuse similar to other opioids including fentanyl, hydromorphone, methadone, oxycodone, oxymorphone, and tapentadol. Morphine Sulfate Injection can be abused and is subject to misuse, addiction, and criminal diversion (see WARNINGS).

All patients treated with opioids require careful monitoring for signs of abuse and addiction, because use of opioid analgesic products carries the risk of addiction even under appropriate medical use. Prescription drug abuse is the intentional non-therapeutic use of a prescription drug, even once, for its rewarding psychological or physiological effects.

Drug addiction is a cluster of behavioral, cognitive, and physiological phenomena that develop after repeated substance use and includes: a strong desire to take the drug, difficulties in controlling its use, persisting in its use despite harmful consequences, a higher priority given to drug use than to other activities and obligations, increased tolerance, and sometimes a physical withdrawal.

"Drug-seeking" behavior is very common in persons with substance abuse disorders. Drug-seeking tactics include emergency calls or visits near the end of office hours, refusal to undergo appropriate examination, testing or referral, repeated "loss" of prescriptions, tampering with prescriptions, and reluctance to provide prior medical records or contact information for other treating physician(s). "Doctor shopping" (visiting multiple prescribers to obtain additional prescriptions) is common among drug abusers and people suffering from untreated addiction. Preoccupation with achieving adequate pain relief can be appropriate behavior in a patient with poor pain control.

Abuse and addiction are separate and distinct from physical dependence and tolerance. Health care providers should be aware that addiction may not be accompanied by concurrent tolerance and symptoms of physical dependence in all addicts. In addition, abuse of opioids can occur in the absence of true addiction.

Morphine Sulfate Injection, like other opioids, can be diverted for non-medical use into illicit channels of distribution. Careful record-keeping of prescribing information, including quantity, frequency, and renewal requests, as required by state and federal law, is strongly advised.

Proper assessment of the patient, proper prescribing practices, periodic re-evaluation of therapy, and proper dispensing and storage are appropriate measures that help to limit abuse of opioid drugs.

Dependence

Both tolerance and physical dependence can develop during chronic opioid therapy. Tolerance is the need for increasing doses of opioids to maintain a defined effect such as analgesia (in the absence of disease progression or other external factors). Tolerance may occur to both the desired and undesired effects of drugs, and may develop at different rates for different effects.

Physical dependence results in withdrawal symptoms after abrupt discontinuation or a significant dosage reduction of a drug. Withdrawal also may be precipitated through the administration of drugs with opioid antagonist activity (e.g., naloxone, nalmefene), mixed agonist/antagonist analgesics (e.g., pentazocine, butorphanol, nalbuphine), or partial agonists (e.g., buprenorphine). Physical dependence may not occur to a clinically significant degree until after several days to weeks of continued opioid usage.

Morphine Sulfate Injection should not be abruptly discontinued in a physically-dependent patient. If Morphine Sulfate Injection is abruptly discontinued in a physically-dependent patient, a withdrawal syndrome may occur. Some or all of the following can characterize this syndrome: restlessness, lacrimation, rhinorrhea, yawning, perspiration, chills, myalgia, and mydriasis. Other signs and symptoms also may develop, including, irritability, anxiety, backache, joint pain, weakness, abdominal cramps, insomnia, nausea, anorexia, vomiting, diarrhea, or increased blood pressure, respiratory rate, or heart rate.

Withdrawal should be treated in a hospital. Usually, it is necessary only to provide supportive care with administration of a tranquilizer to suppress anxiety. Severe symptoms of withdrawal may require administration of a replacement narcotic.

Infants born to mothers physically dependent on opioids will also be physically dependent and may exhibit respiratory difficulties and withdrawal signs (see PRECAUTIONS).

OVERDOSAGE

Clinical Presentation

Acute overdose with Morphine Sulfate Injection can be manifested by respiratory depression (a decrease in respiratory rate and/or tidal volume, Cheyne-Stokes respiration, cyanosis), somnolence progressing to stupor or coma, skeletal muscle flaccidity, cold and clammy skin, constricted pupils, and, in some cases, pulmonary edema, bradycardia, hypotension, partial or complete airway obstruction, atypical snoring, and death. Marked mydriasis rather than miosis may be seen with hypoxia in overdose situations (see CLINICAL PHARMACOLOGY). In severe overdosage, particularly by the intravenous route, apnea, circulatory collapse, cardiac arrest, and death may occur.

Treatment of Overdose

In case of overdose, priorities are the reestablishment of a patent and protected airway and institution of assisted or controlled ventilation, if needed. Employ supportive measures (including oxygen and vasopressors) in the management of circulatory shock and pulmonary edema as indicated. Cardiac arrest or arrhythmias will require advanced life-support techniques. If depressed respiration is associated with muscular rigidity, an intravenous neuromuscular blocking agent may be required to facilitate assisted or controlled respiration.

The opioid antagonists, naloxone or nalmefene, are specific antidotes to respiratory depression resulting from opioid overdose. For clinically significant respiratory or circulatory depression secondary to morphine sulfate overdose, administer an opioid antagonist. Opioid antagonists should not be administered in the absence of clinically significant respiratory or circulatory depression secondary to morphine sulfate overdose.

Because the duration of opioid reversal is expected to be less than the duration of action of morphine in Morphine Sulfate Injection, carefully monitor the patient until spontaneous respiration is reliably re-established. If the response to an opioid antagonist is suboptimal or only brief in nature, administer additional antagonist as directed by the product's prescribing information.

In an individual physically dependent on opioids, administration of the recommended dosage of the antagonist will precipitate an acute withdrawal syndrome. The severity of the withdrawal symptoms experienced will depend on the degree of physical dependence and the dose of the antagonist administered. If a decision is made to treat serious respiratory depression in the physically dependent patient, administration of the antagonist should begin with care and by titration with smaller than usual doses of the antagonist.

Oxygen, intravenous fluids, vasopressors, and other supportive measures should be employed as indicated. In cases of oral overdose, the stomach should be evacuated by emesis or gastric lavage if treatment can be instituted within 2 hours following ingestion. The patient should be observed closely for a rise in temperature or pulmonary complications that may signal the need for institution of antibiotic therapy.

DOSAGE AND ADMINISTRATION

THESE PRODUCTS ARE INTENDED FOR SLOW INTRAVENOUS USE ONLY. RAPID INTRAVENOUS ADMINISTRATION MAY RESULT IN CHEST WALL RIGIDITY. NOT FOR INTRATHECAL OR EPIDURAL USE.

For Relief of Pain and as Pre-anesthetic

The usual adult dose of 10 mg every 4 hours, depending on the severity of the condition and the patient's response. The usual individual dose range is 5 to 15 mg. The usual daily dose range is 12 to 120 mg.

Usual Pediatric Dose

Analgesic - Intravenous, 50 to 100 µg (0.05 to 0.1 mg) per kg of body weight, administered very slowly. Not to exceed 10 mg per dose.

For Open-Heart Surgery

Large doses (0.5 to 3 mg/kg) of morphine are administered intravenously as the sole anesthetic or with a suitable anesthetic agent. The patients are given oxygen and cardiovascular function is not depressed by morphine, as long as adequate ventilation is maintained.

For Severe Chronic Pain Associated with Terminal Cancer

Continuous Intravenous infusion

Prior to the initiation of the morphine infusion (in concentrations between 0.2 to 1 mg/mL), a loading dose of 15 mg or higher of morphine sulfate may be administered by intravenous push to alleviate pain.

The infusion dosage range is 0.8 mg/hr to 80 mg/hr, though doses of up to 144 mg/hr have been used. Thus, for the 1 mg/mL solution, the infusion may be run from 0.8 mL /hr to 80 mL /hr, and for the 0.5 mg/mL solution, the infusion may be run from 1.6 mL /hr to 160 mL /hr.

A constant infusion rate must be maintained with an infusion pump in order to assure proper dosage control. Care must be taken to avoid overdosage (respiratory depression) or abrupt cessation of therapy, which may give rise to withdrawal symptoms.

Administration of Morphine Sulfate Injection should be limited to use by those familiar with the management of respiratory depression.

NOTE: Parenteral drug products should be inspected visually for particulate matter and discoloration prior to administration, whenever solution and container permit.

EXAMPLES OF INFUSION PREPARATION:

Concentrate | Diluent | Final Concentration
Morphine Sulfate Injection, USP | Dextrose 5% in Water | Morphine Sulfate
25 mg/mL
10 mL | 490 mL | 0.5 mg/mL
20 mL | 480 mL | 1.0 mg/mL
40 mL | 960 mL | 1.0 mg/mL
Morphine Sulfate Injection, USP
50 mg/mL
10 mL | 990 mL | 0.5 mg/mL
20 mL | 980 mL | 1.0 mg/mL

HOW SUPPLIED

Morphine Sulfate Injection, USP, is available in glass fliptop vials as follows:

25 mg/mL Morphine Sulfate Injection, USP, Preservative Free (no bacteriostat or antioxidant added).

Single-dose vials. [Contains no antimicrobial preservatives.]

Unit of Sale | Concentration
NDC 0409-1135-02 Carton of 1 Single-dose Fliptop Vial | 250 mg/10 mL (25 mg/mL)

50 mg/mL Morphine Sulfate Injection, USP (no bacteriostat added).

Single-dose vials.

Unit of Sale | Concentration
NDC 0409-1134-03 Carton of 1 Single-dose Fliptop Vial | 1,000 mg/20 mL (50 mg/mL)
NDC 0409-1134-05 Carton of 1 Single-dose Fliptop Vial | 2,500 mg/50 mL (50 mg/mL)

FOR INTRAVENOUS USE ONLY AFTER DILUTION.

NOT FOR DIRECT INJECTION.

THESE PRODUCTS ARE INTENDED FOR INTRAVENOUS USE ONLY.

NOT INTENDED FOR INTRATHECAL OR EPIDURAL USE.

Storage

Store at 20 to 25°C (68 to 77°F). [See USP Controlled Room Temperature.] Morphine sulfate solutions may darken with age. Do not use if injection is darker than pale yellow, discolored in any other way, or contains a precipitate. Do not heat-sterilize the Preservative Free (antioxidant free) formula.

PROTECT FROM LIGHT

Hospira, Inc., Lake Forest, IL 60045 USA

LAB-1040-4.0
Revised September 2021

PRINCIPAL DISPLAY PANEL - 1000 mg/20 mL Vial Label

20 mL
Single-dose Fliptop Vial
NDC 0409-1134-03
Rx only

MORPHINE
Sulfate Inj., USP
CII

1000 mg/20 mL* (50 mg/mL)*

FOR INTRAVENOUS USE ONLY.

NOT FOR INTRATHECAL OR EPIDURAL USE.
CAUTION: FOR DILUTION ONLY.
NOT FOR DIRECT INJECTION.
WARNING: Contains Sulfites

Hospira, Inc., Lake Forest, IL 60045 USA

Hospira

PRINCIPAL DISPLAY PANEL - 1000 mg/20 mL Vial Carton

1 x 20 mL
Single-dose
Fliptop Vial
NDC 0409-1134-03
Rx only

MORPHINE
Sulfate Inj., USP
CII

1000 mg/20 mL* (50 mg/mL)*

FOR INTRAVENOUS USE ONLY.

NOT FOR INTRATHECAL OR EPIDURAL USE.

CAUTION: FOR DILUTION ONLY.

NOT FOR DIRECT INJECTION.

WARNING: Contains Sulfites

Hospira

PRINCIPAL DISPLAY PANEL - 2500 mg/50 mL Vial Label

NDC 0409-1134-05

50 mL
Single-dose Fliptop Vial
Rx only

MORPHINE
Sulfate Inj., USP
CII

2500 mg/50 mL* (50 mg/mL*)

FOR INTRAVENOUS USE ONLY.

NOT FOR INTRATHECAL OR EPIDURAL USE.
CAUTION: FOR DILUTION ONLY.
NOT FOR DIRECT INJECTION.
WARNING: Contains Sulfites

Hospira, Inc., Lake Forest, IL 60045 USA

Hospira

PRINCIPAL DISPLAY PANEL - 2500 mg/20 mL Vial Carton

1 x 50 mL
Single-dose
Fliptop Vial
NDC 0409-1134-05
Rx only

MORPHINE
Sulfate Inj., USP
CII

2500 mg/50 mL*(50 mg/mL*)

FOR INTRAVENOUS USE ONLY.

NOT FOR INTRATHECAL OR EPIDURAL USE.

CAUTION: FOR DILUTION ONLY.

NOT FOR DIRECT INJECTION.

WARNING: Contains Sulfites

Hospira

PRINCIPAL DISPLAY PANEL - 250 mg Vial Label

10 mL Fill
NDC 0409-1135-02

Single-dosage Fliptop Vial

MORPHINE
Sulfate Inj., USP
CII

(25 mg/mL)* 250 mg*

PRESERVATIVE FREE

WARNING: MAY BE HABIT FORMING.
CAUTION: FOR DILUTION ONLY.
NOT FOR DIRECT INJECTION.

Rx only

HOSPIRA, INC., LAKE FOREST, IL 60045 USA

PRINCIPAL DISPLAY PANEL - 250 mg Vial Carton

One Unit/NDC 0409-1135-02

10 mL Fill

Single-dosage
Fliptop Vial

MORPHINE
Sulfate
Inj., USP
CII

(25 mg/mL)*

250 mg*
Rx only

PRESERVATIVE FREE

WARNING: MAY BE HABIT FORMING.

CAUTION: FOR DILUTION ONLY.
NOT FOR DIRECT INJECTION.

Hospira

Hospira, Inc.
Lake Forest, IL 60045 USA